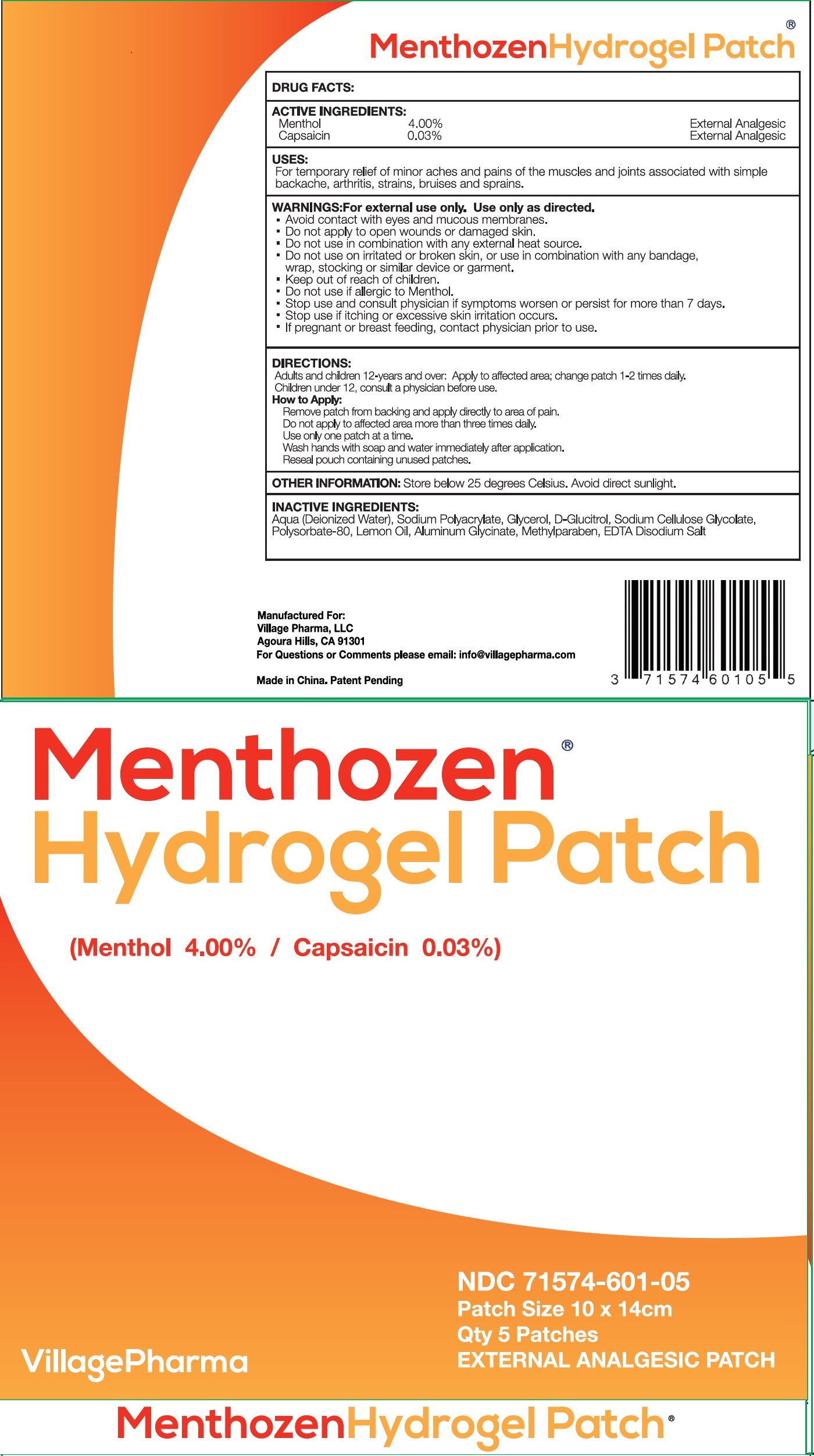 DRUG LABEL: Menthozen Hydrogel
NDC: 71574-601 | Form: PATCH
Manufacturer: Village Pharma LLC
Category: otc | Type: HUMAN OTC DRUG LABEL
Date: 20260101

ACTIVE INGREDIENTS: MENTHOL, UNSPECIFIED FORM 40 mg/1 g; CAPSAICIN 0.3 mg/1 g
INACTIVE INGREDIENTS: WATER; GLYCERIN; CARBOXYMETHYLCELLULOSE SODIUM, UNSPECIFIED; POLYSORBATE 80; LEMON OIL, COLD PRESSED; DIHYDROXYALUMINUM AMINOACETATE ANHYDROUS; METHYLPARABEN; EDETATE DISODIUM

Menthozen Hydrogel Patch

ACTIVE INGREDIENTS:

Menthol 4.00%

Capsaician 0.03%

PURPOSE

External Analgesic

USES:

For temporary relief of minor aches and pains of the muscles and joints associated with simple backache, arthritis, strains, bruises and sprains.

WARNINGS:

For external use only. Use only as directed.

- Avoid contact with eyes and mucous membranes.
- Do not apply to open wounds or damaged skin.

Do not use

- in combination with any external heat source.
- Do not use on irritated or broken skin, or use in combination with any bandage, wrap, stocking or similar device or garment.

Keep out of reach of children.

- Do not use if allergic to Menthol.

Stop use and consult physician

- if symptoms worsen or persist for more than 7 days.
- Stop use if itching or excessive skin irritation occurs.

If pregnant or breast feeding,

- contact physician prior to use

DIRECTIONS:

Adults and children 12-years and over: Apply to affected area; change patch 1-2 times dily.

Children under 12, consult a physician before use.

: How to Apply

Remove patch from backing and apply directly to area of pain.

Do not apply to affected area more than three times daily.

Use only one patch at a time.

Wash hands with soap and water immediately after application.

Reseal pouch containg unused patches.

OTHER INFORMATION:

Store below 25 degrees Celsius. Avoid direct sunlight.

INACTIVE INGREDIENTS:

Aqua (Deionized Water), Sodium Polyacrylate, Glycerol, D-Glucitrol, Sodium Cellulose Glycolate, Polysorbate-80, Lemon Oil, Aluminum Glycinate, Methylparaben, EDTA Disodium Salt